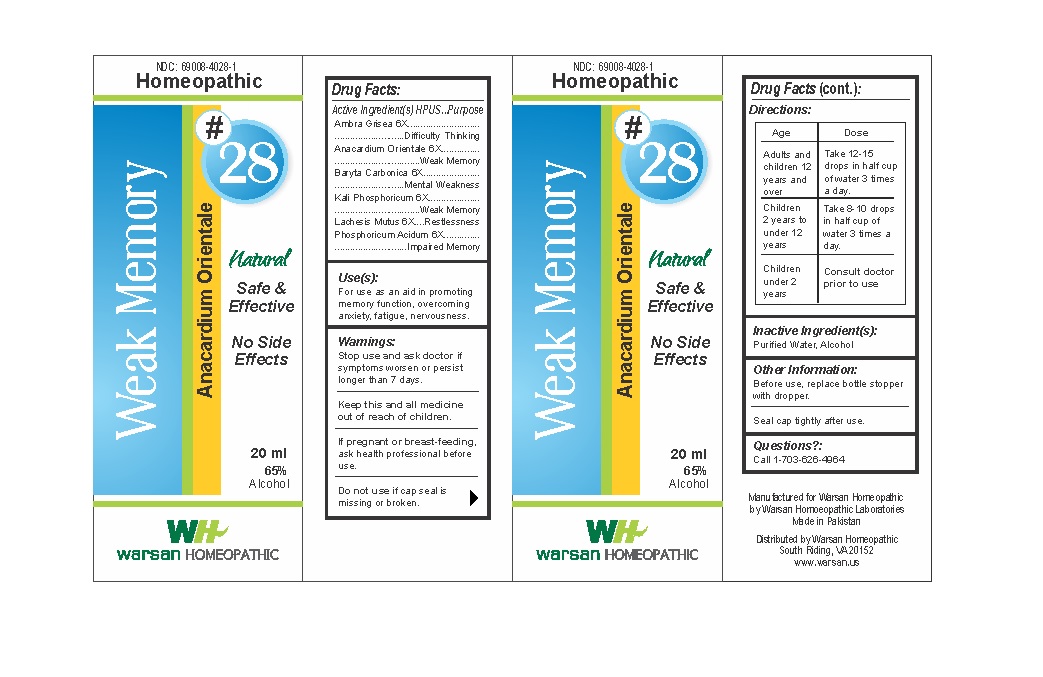 DRUG LABEL: Combination Remedy 28 - Weak Memory
NDC: 69008-4028 | Form: SOLUTION/ DROPS
Manufacturer: Warsan Homoeopathic Laboratories
Category: homeopathic | Type: HUMAN OTC DRUG LABEL
Date: 20171225

ACTIVE INGREDIENTS: BARIUM CARBONATE 6 [hp_X]/1 mL; POTASSIUM PHOSPHATE, DIBASIC 6 [hp_X]/1 mL; AMBERGRIS 6 [hp_X]/1 mL; PHOSPHORIC ACID 6 [hp_X]/1 mL; SEMECARPUS ANACARDIUM JUICE 6 [hp_X]/1 mL; LACHESIS MUTA VENOM 6 [hp_X]/1 mL
INACTIVE INGREDIENTS: ALCOHOL; WATER

Stop use and ask doctor if symptoms worsen or persist longer than 7 days.

If pregnant or breast-feeding, ask health professional before use.

Do not use if tamper evident seal is missing or broken.

Keep out of reach of children.

ACTIVE INGREDIENT

Ambra Grisea 6X
Anacardium Orientale 6X
Baryta Carbonica 6X
Kali Phosphoricum 6X
Lachesis Mutus 6X
Phosphoricum Acidum 6X

PURPOSE

For use as an aid in promoting memory function, overcoming anxiety, fatigue, nervousness. .

INACTIVE INGREDIENT

Purified Water

Alcohol

DOSAGE AND ADMINISTRATION

Adults and children 12 years and older: Take 10-15 drops in half cup of water 3 times a day.

Children 2 years to under 12 years: Take 8-10 drops in half cup of water of 3 times a day.

Children under 2 years: Consult doctor prior to use.

INDICATIONS AND USAGE

For use as an aid in promoting memory function, overcoming anxiety, fatigue, nervousness. .